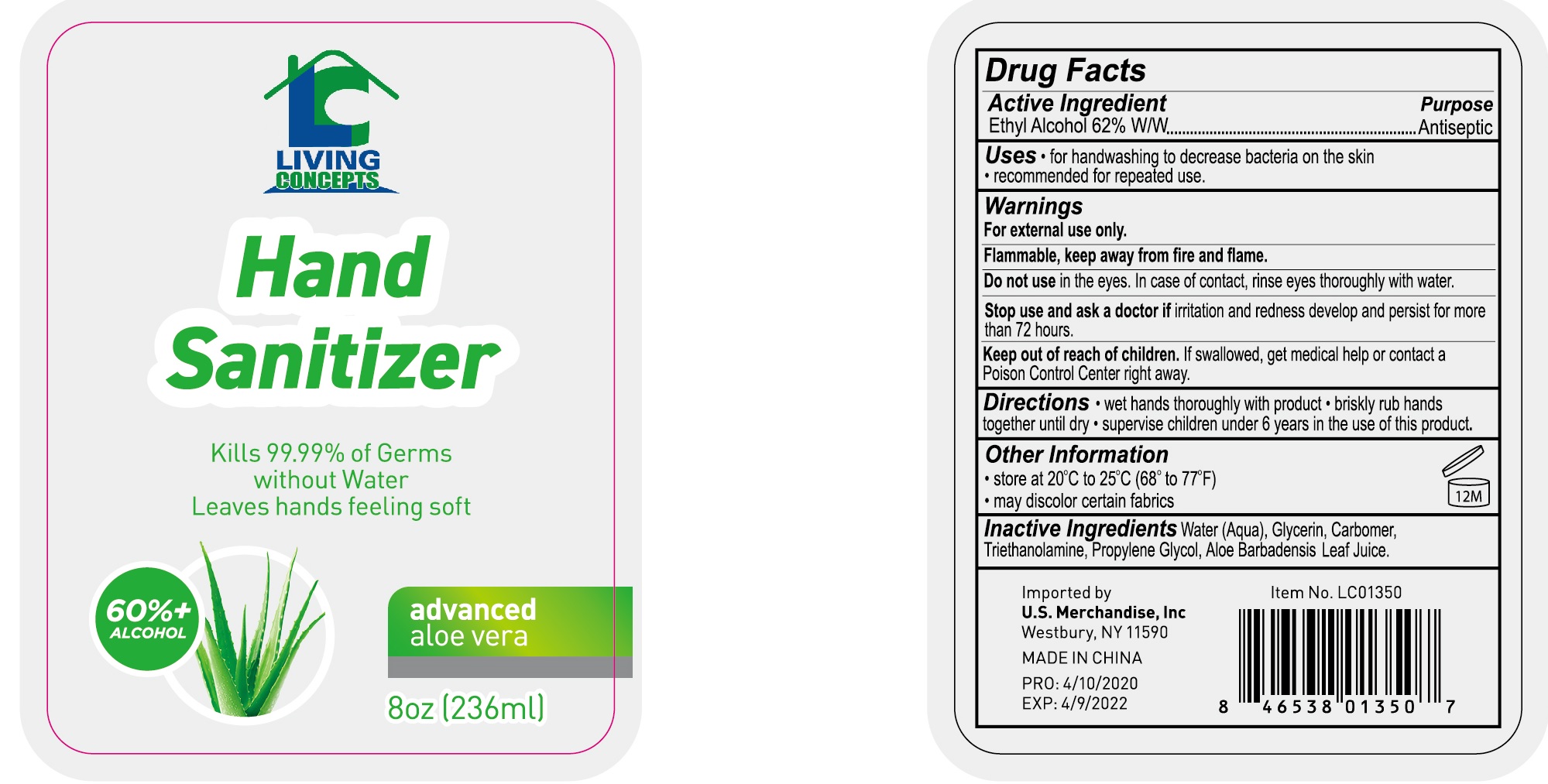 DRUG LABEL: Living Concepts Hand Sanitizer advanced aloe vera
NDC: 74149-010 | Form: SOLUTION
Manufacturer: Yiwu Yangjie Daily Chemicals Co.,Ltd.
Category: otc | Type: HUMAN OTC DRUG LABEL
Date: 20200413

ACTIVE INGREDIENTS: alcohol 62 mL/100 mL
INACTIVE INGREDIENTS: WATER; PROPYLENE GLYCOL; ALOE VERA LEAF; CARBOMER 934; GLYCERIN; .ALPHA.-TOCOPHEROL ACETATE; TROLAMINE

Drug facts

Active ingredient Purpose

Ethyl Alcohol 62% ... Antiseptic

PURPOSE

- help decrease bacteria on the hands
- Recommended for repeated use.

WARNINGS

For external use only.
Flammable. Keep away from fire or flame.

Do not use in the eyes. In case of contact, rinse eyes thoroughly with water.

Stop use and ask a doctor If irritation and redness and persist for more than 72 hours.

KEEP OUT OF REACH OF CHILDREN

If swallowed, get medical help or contact a Poison Control Center right away.

INDICATIONS AND USAGE

- Wet hands throughly with product
- Briskly rub hands together until dry
- supervise children under 6 years in the use of this product.

Other information:

- Store under 20℃ to 25 ℃ （68 - 77℉）
- May discolor ceertain fabrics

INACTIVE INGREDIENT

Water (Aqua), Glycerin, Carbomer, Triethanolamine, Propylene Glycol, Aloe Barbadensis Leaf Juice